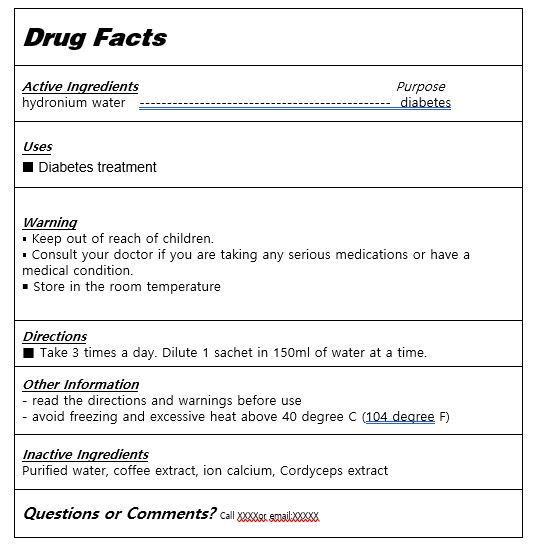 DRUG LABEL: coffeerazzi minerang dutchcoffee
NDC: 81016-0008 | Form: LIQUID
Manufacturer: AML Bio Co., Ltd.
Category: otc | Type: HUMAN OTC DRUG LABEL
Date: 20240123

ACTIVE INGREDIENTS: ATORVASTATIN CALCIUM ANHYDROUS 3 g/100 mL
INACTIVE INGREDIENTS: WATER

Drug Facts

ACTIVE INGREDIENT

mineral complex

PURPOSE

diabetes treatment

KEEP OUT OF REACH OF THE CHILDREN

INDICATIONS AND USAGE

Take 3 times a day. Dilute 1 sachet in 150ml of water at a time.

▪ Keep out of reach of children.

▪ Consult your doctor if you are taking any serious medications or have a medical condition.

￭ Store in the room temperature

DOSAGE AND ADMINISTRATION

for oral use only

INACTIVE INGREDIENT

Purified water, ion calcium, zinc, cordyceps extract, water-soluble chitosan